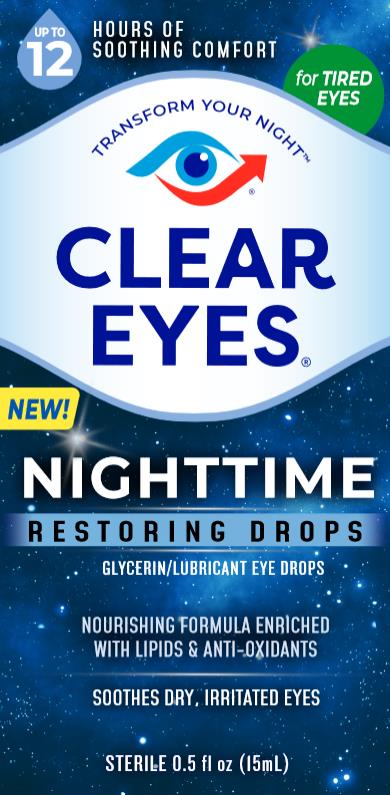 DRUG LABEL: Clear Eyes Nighttime
NDC: 67172-505 | Form: SOLUTION/ DROPS
Manufacturer: Prestige Brands Holdings, Inc.
Category: otc | Type: HUMAN OTC DRUG LABEL
Date: 20240111

ACTIVE INGREDIENTS: GLYCERIN 2.5 mg/1 mL
INACTIVE INGREDIENTS: BORIC ACID; PHOSPHATIDYLCHOLINE, SOYBEAN; POLIHEXANIDE; WATER; SODIUM BORATE; SODIUM CHLORIDE; HYALURONATE SODIUM; .ALPHA.-TOCOPHEROL ACETATE

Clear Eyes Nighttime

Drug Facts

Active ingredient

Glycerin 0.25%

Purpose

Lubricant

Uses

- For use as a protectant against further irritation or to relieve dryness of the eye.
- For the temporary relief of burning and irritation due to dryness of the eye.

Warnings

For external use only.

Do not use

if solution changes color or becomes cloudy.

Ask a doctor before use

if you have narrow angle glaucoma.

When using this product

- To avoid contamination, do not touch tip to any surface.
- Replace cap after using.
- Overuse may produce increased redness of the eye.
- Pupils may become enlarged temporarily.

Stop use and ask a doctor if:

- you experience eye pain
- you experience changes in vision
- you experience continued redness or irritation of the eye
- the condition worsens
- symptoms last for more than 72 hours

Keep out of reach of children.

If swallowed, get medical help or contact a Poison Control Center (1-800-222-1222) right away.

Directions

Put 1 to 2 drops in the affected eye(s) as needed.

Other information

- Store at room temperature.
- Remove contact lenses before using.
- Keep carton for future reference.

Inactive ingredients

boric acid, phosphatidylcholine, polyhexanide, purified water, sodium borate, sodium chloride, sodium hyaluronate, tocopherol acetate

Questions?

1-877-274-1787 Cleareyes.com

PRINCIPAL DISPLAY PANEL

Clear eyes ®
NIGHTTIME
Restoring Drops

Glycerin / Lubricant Eye Drops

Sterile 0.5 FL OZ (15 mL)